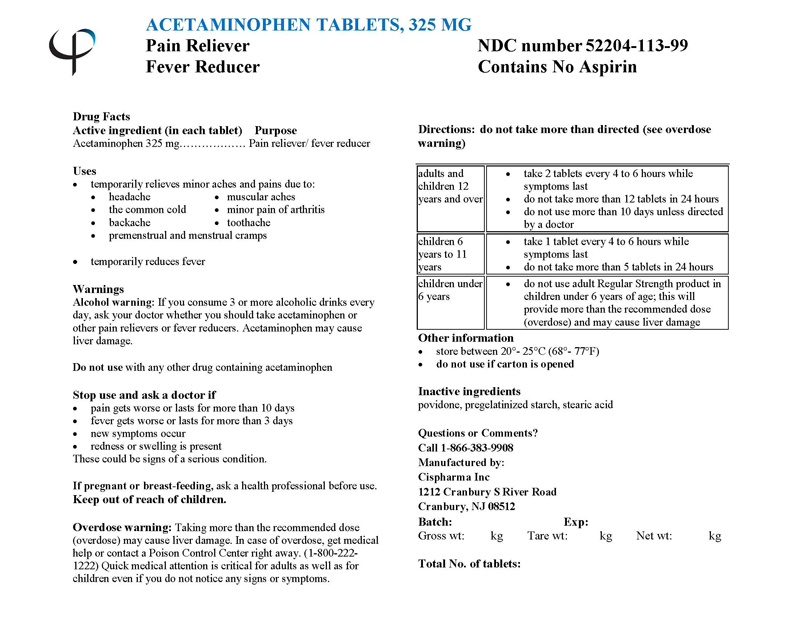 DRUG LABEL: ACETAMINOPHEN
NDC: 52204-113 | Form: TABLET
Manufacturer: Cispharma, Inc
Category: otc | Type: HUMAN OTC DRUG LABEL
Date: 20110328

ACTIVE INGREDIENTS: ACETAMINOPHEN 325 mg/1 1
INACTIVE INGREDIENTS: POVIDONE; STARCH, PREGELATINIZED CORN; STEARIC ACID

ACETAMINOPHEN TABLETS, 325mg

Drug Facts

Active ingredient (in each tablet)

Acetaminophen .............................. 325 mg

PURPOSE

Pain Reliever/ Fever Reducer

Uses

Temporarily relieves minor aches and pains due to:

- headache
- the common cold
- backache
- muscular aches
- minor pain of arthritis
- toothache
- premenstrual and menstrual cramps

temporarily reduces fever

Warnings

Alcohol warning: If you consume 3 or more alcoholic drinks every day, ask your doctor whether you should take acetaminophen or other pain relievers or fever reducers. Acetaminophen may cause liver damage.

Do not use with any other drug containing acetaminophen

Stop use and ask a doctor if

- pain gets worse or lasts for more than 10 days
- fever gets worse or lasts for more than 3 days
- new symptoms occur
- redness or swelling is present

These could be signs of a serious condition.

INDICATIONS AND USAGE

Indicated for pain relief.

PREGNANCY OR BREAST FEEDING

If pregnant or breast-feeding, ask a health professional before use.

Keep out of reach of children.

Overdose Warning:

Taking more than the recommended dose (overdose) may cause liver damage. In case of overdose, get medical help or contact a Poison Control Center right away. (1-800-222-1222) Quick medical attention is critical for adults as well as for children even if you do not notice any signs or symptoms.

Directions: do not take more than directed (see overdose warning)

adults and children 12 years and over | - take 2 tablets every 4 to 6 hours while symptoms last - do not take more than 12 tablets in 24 hours - do not use more than 10 days unless directed by a doctor
children 6 years to 11 years | - take 1 tablet every 4 to 6 hours while symptoms last - do not take more than 5 tablets in 24 hours
children under 6 years | - do not use adult Regular Strength product in children under 6 years of age; this will provide more than the recommended dose (overdose) and may cause liver damage

Other Information

- store between 20°- 25°C (68°- 77°F)
- do not use if carton is opened

Inactive Ingredients

povidone, pregelatinized starch, stearic acid

Questions or Comments?
Call 1-866-383-9908

Manufactured by:

Cispharma Inc
1212 Cranbury S River Road
Cranbury, NJ 08512